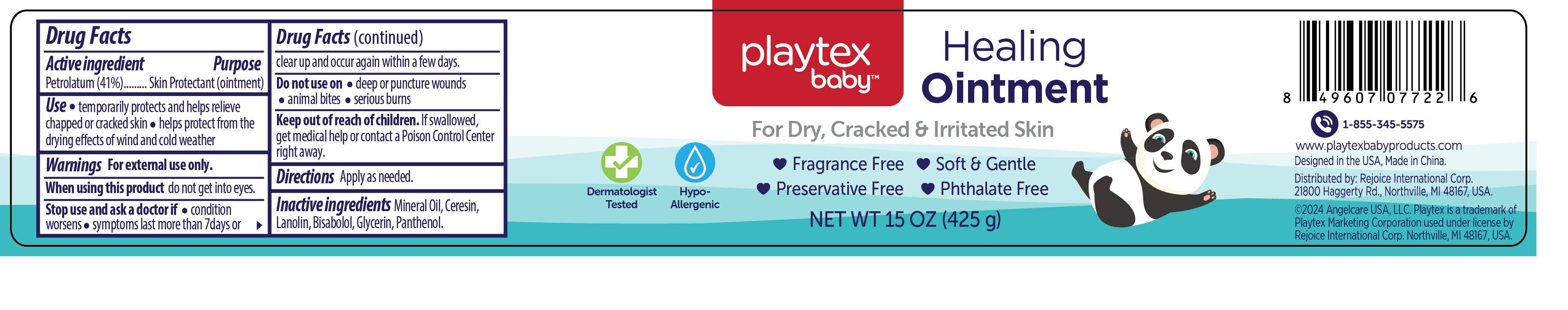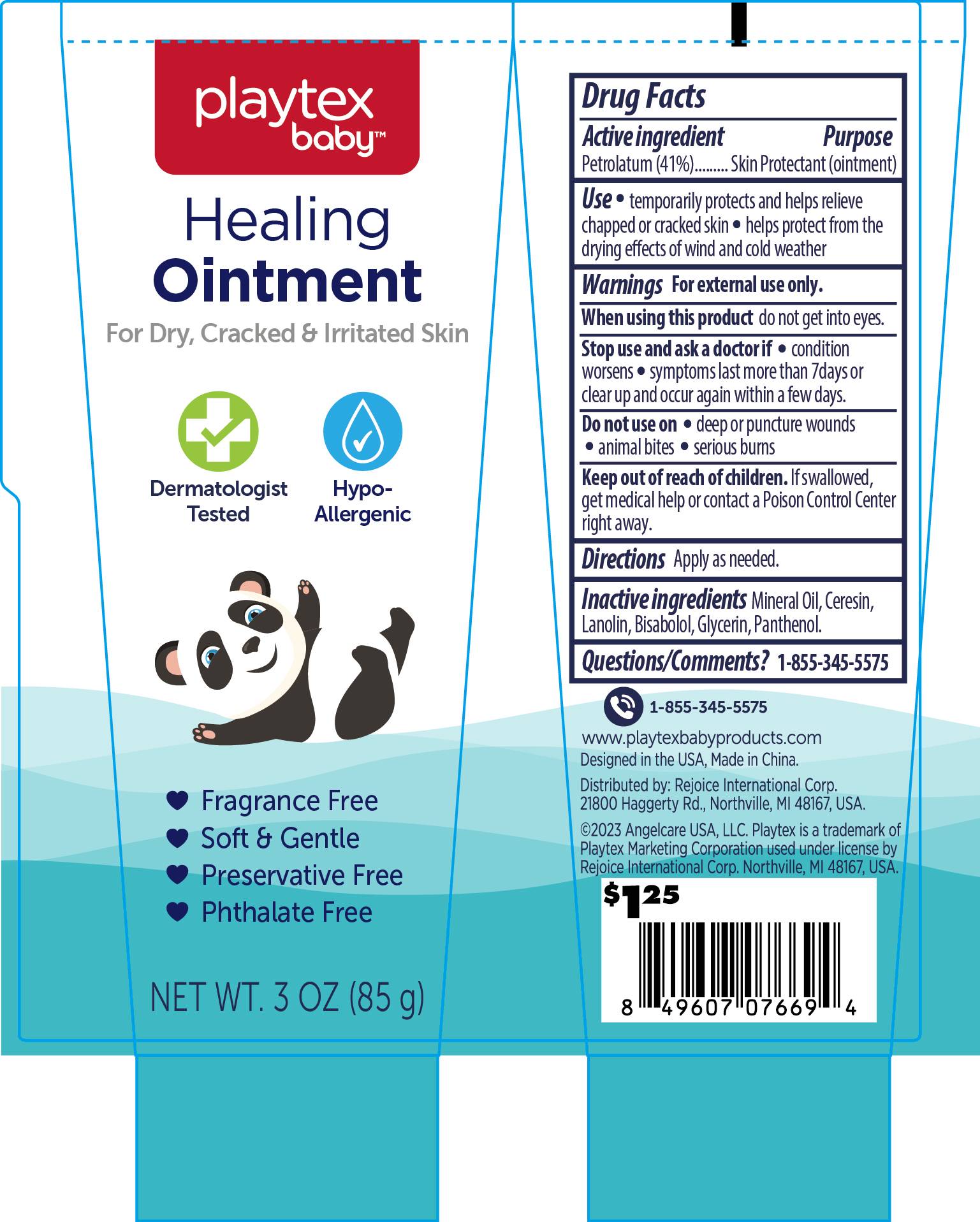 DRUG LABEL: Healing Cream 3oz
NDC: 58503-201 | Form: OINTMENT
Manufacturer: China Ningbo Shangge Cosmetics Technology Corp.
Category: otc | Type: HUMAN OTC DRUG LABEL
Date: 20240911

ACTIVE INGREDIENTS: PETROLATUM 41 g/100 g
INACTIVE INGREDIENTS: MINERAL OIL; GLYCERIN; CERESIN; LANOLIN; LEVOMENOL; PANTHENOL

Active ingredient

Petrolatun 41%

Purpose

Skin Protectant (Ointment)

Use

temporarily protects and helps relieve chapped or cracked skin
helps protect from the drying effects of wind and cold weather

Warnings

For external use only

When using this product do not get into eyes.

Stop use and ask a doctor if

condition worsens
symptoms last more than 7days or clear up and occur again within a few days.

Do not use on

deep or puncture wounds
animal bites
serious burns

Keep out of reach of children

If swallowed, get medical help or contact a Poison Control Center right away.

Inactive ingredients

Mineral Oil
Ceresin
Lanolin
Bisabolol
Glycerin
Panthenol

Directions

Apply as needed.

Use

temporarily protects and helps relieve chapped or cracked skin
helps protect from the drying effects of wind and cold weathe